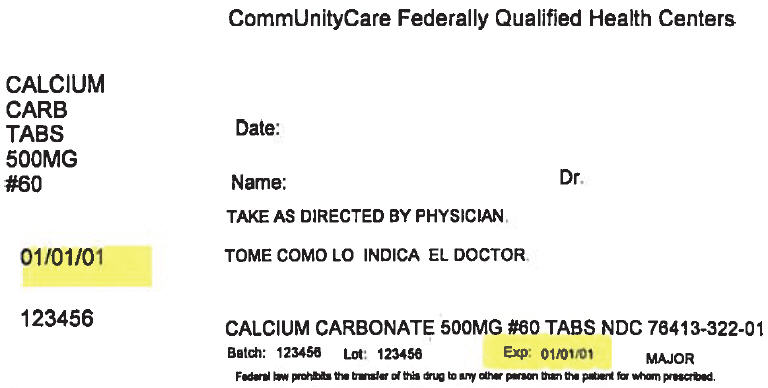 DRUG LABEL: Oyster Shell Calcium
NDC: 76413-322 | Form: TABLET
Manufacturer: Central Texas Community Health Centers
Category: other | Type: DIETARY SUPPLEMENT
Date: 20170915

ACTIVE INGREDIENTS: Calcium carbonate 500 mg/1 1
INACTIVE INGREDIENTS: Croscarmellose sodium; Microcrystalline Cellulose; HYPROMELLOSE, UNSPECIFIED; Polydextrose; Titanium Dioxide; Talc; Sodium Lauryl Sulfate

OYSTER SHELL CALCIUM

STATEMENT OF IDENTITY

Supplement Facts
Serving Size: 1 Tablet
Amount Per Serving | % Daily Value
Calcium (as Oyster Shell) | 500 mg. | 50%

OTHER INGREDIENTS: Croscarmellose Sodium, Microcrystalline Cellulose, Hypromellose, Polydextrose, Titanium Dioxide, Soy Polysaccharide, Talc, Sodium Lauryl Sulfate and Triglycerides.

Contains: Soy and Shellfish

DIRECTIONS

For adults, take one (1) tablet daily preferably with a meal. As a reminder, discuss the supplements and medications you take with your health care providers.

WARNING

If you are pregnant, nursing, taking any medications or planning any medical procedure, consult your doctor before use. Discontinue use and consult your doctor if any adverse reactions occur.

FREE OF

Yeast, wheat, milk or milk derivatives, lactose, sugar, preservatives, artificial color, artificial flavor, sodium (less than 5 mg per serving).

HEALTH CLAIM

Adequate calcium throughout life, as part of a well balanced diet, may reduce the risk of osteoporosis*

* THIS STATEMENT HAS NOT BEEN EVALUATED BY THE FOOD AND DRUG ADMINISTRATION. THIS PRODUCT IS NOT INTENDED TO DIAGNOSE, TREAT, CURE, OR PREVENT ANY DISEASE.

SAFE HANDLING WARNING

KEEP OUT OF THE REACH OF CHILDREN. STORE AT ROOM TEMPERATURE AND AVOID EXCESSIVE HEAT.

TAMPER RESISTANT: DO NOT USE IF SEAL UNDER CAP IS BROKEN OR MISSING.

HEALTH CLAIM

Distributed by: MAJOR® PHARMACEUTICALS
31778 Enterprise Drive, Livonia, MI 48150, USA
Questions or Comments? (800) 616-2471

LOT # & EXP. DATE:
M-29 Rev. 04/16
11098-04-16

PRINCIPAL DISPLAY PANEL - 500 mg Tablet Bottle Label

CommUnityCare Federally Qualified Health Centers

CALCIUM
CARB
TABS
500MG
#60

Date:

Name:
Dr.

TAKE AS DIRECTED BY PHYSICIAN.

01/01/01

123456

CALCIUM CARBONATE 500MG #60 TABS NDC 76413-322-01

Batch:
123456
Lot:
123456
Exp:
01/01/01

MAJOR

Federal law prohibits the transfer of this drug to any other person than the patient for whom prescribed.